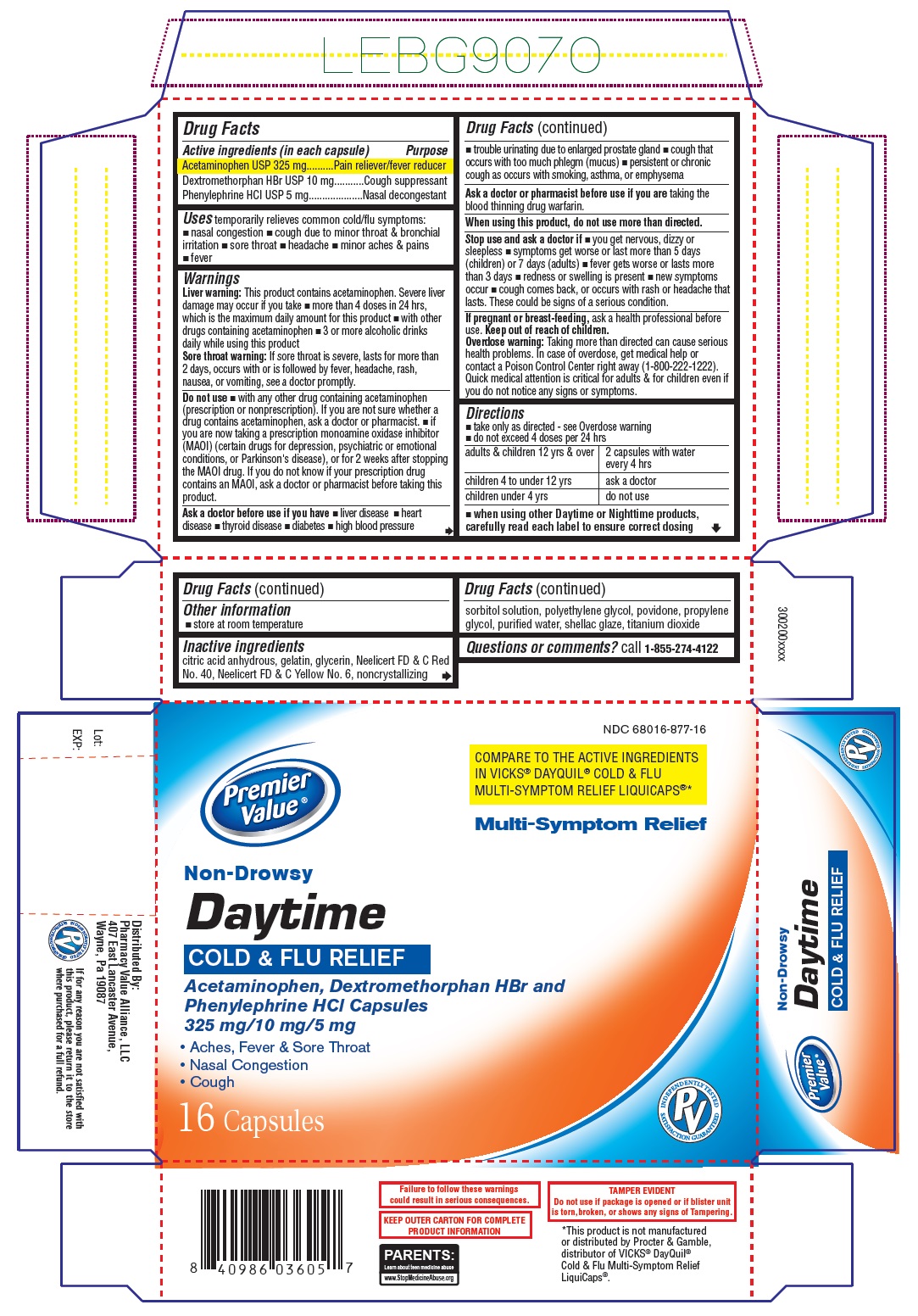 DRUG LABEL: DAYTIME COLD AND FLU MULTI-SYMPTOM RELIEF
NDC: 68016-877 | Form: CAPSULE
Manufacturer: Chain Drug Consortium, LLC
Category: otc | Type: Human OTC Drug Label
Date: 20241024

ACTIVE INGREDIENTS: ACETAMINOPHEN 325 mg/1 1; DEXTROMETHORPHAN HYDROBROMIDE 10 mg/1 1; PHENYLEPHRINE HYDROCHLORIDE 5 mg/1 1
INACTIVE INGREDIENTS: ANHYDROUS CITRIC ACID; GELATIN, UNSPECIFIED; GLYCERIN; FD&C RED NO. 40; FD&C YELLOW NO. 6; SORBITOL; POLYETHYLENE GLYCOL, UNSPECIFIED; POVIDONE, UNSPECIFIED; PROPYLENE GLYCOL; WATER; SHELLAC; TITANIUM DIOXIDE

DAYTIME COLD AND FLU
Multi-Symptom Relief

Drug Facts

Active ingredients (in each capsule)
Acetaminophen USP 325 mg
Dextromethorphan HBr USP 10 mg
Phenylephrine HCl USP 5 mg

Purpose

Pain reliever/fever reducer
Cough suppressant
Nasal decongestant

Uses

temporarily relieves common cold/flu symptoms:

- nasal congestion
- cough due to minor throat & bronchial irritation
- sore throat
- headache
- minor aches & pains
- fever

Warnings

Liver warning: This product contains acetaminophen. Severe liver damage may occur if you take

- more than 4 doses in 24 hrs, which is the maximum daily amount for this product
- with other drugs containing acetaminophen
- 3 or more alcoholic drinks daily while using this product

Sore throat warning: If sore throat is severe, lasts for more than 2 days, occurs with or is followed by fever, headache, rash, nausea, or vomiting, see a doctor promptly.

Do not use

- with any other drug containing acetaminophen (prescription or nonprescription). If you are not sure whether a drug contains acetaminophen, ask a doctor or pharmacist.
- if you are now taking a prescription monoamine oxidase inhibitor (MAOI) (certain drugs for depression, psychiatric or emotional conditions, or Parkinson's disease), or for 2 weeks after stopping the MAOI drug. If you do not know if your prescription drug contains an MAOI, ask a doctor or pharmacist before taking this product.

Ask a doctor before use if you have

- liver disease
- heart disease
- thyroid disease
- diabetes
- high blood pressure
- trouble urinating due to enlarged prostate gland
- cough that occurs with too much phlegm (mucus)
- persistent or chronic cough as occurs with smoking, asthma, or emphysema

Ask a doctor or pharmacist before use if you are

taking the blood thinning drug warfarin

When using this product,

do not use more than directed.

Stop use and ask a doctor if

- you get nervous, dizzy or sleepless
- symptoms get worse or last more than 5 days (children) or 7 days (adults)
- fever gets worse or lasts more than 3 days
- redness or swelling is present
- new symptoms occur
- cough comes back, or occurs with rash or headache that lasts.

These could be signs of a serious condition.

If pregnant or breast-feeding,

ask a health professional before use.

Keep out of reach of children.

Overdose warning:
Taking more than directed can cause serious health problems. In case of overdose, get medical help or contact a Poison Control Center right away (1-800-222-1222). Quick medical attention is critical for adults & for children even if you do not notice any signs or symptoms.

Directions

- take only as directed – see Overdose warning
- do not exceed 4 doses per 24 hours

adults & children 12 yrs & over | 2 capsules with water every 4 hrs
children 4 to under 12 yrs | ask a doctor
children under 4 yrs | do not use

when using other Daytime or Nighttime products, carefully read each label to ensure correct dosing

Other information

- store at room temperature

Inactive ingredients

citric acid anhydrous, gelatin, glycerin, Neelicert FD & C Red No. 40, Neelicert FD & C Yellow No. 6, noncrystallizing sorbitol solution, polyethylene glycol, povidone, propylene glycol, purified water, shellac glaze, titanium dioxide

Questions or comments?

call 1-855-274-4122
Distributed by:
Pharmacy Value Alliance, LLC

407 East Lancaster Avenue,

Wayne, Pa 19087

PACKAGE LABEL-PRINCIPAL DISPLAY PANEL - 16 capsule Bottle

NDC 68016-877-16

Premier Value

COMPARE TO THE ACTIVE INGREDIENTS
IN VICKS® DAYQUIL® COLD & FLU
MULTI-SYMPTOM RELIEF LIQUICAPS®*

Multi-Symptom Relief

Daytime
COLD & FLU RELIEF

Acetaminophen, Dextromethorphan HBr and

Phenylephrine HCl Capsules

325 mg/10 mg/5 mg

- Aches, Fever & Sore Throat
- Nasal Congestion
- Cough

16 Capsules